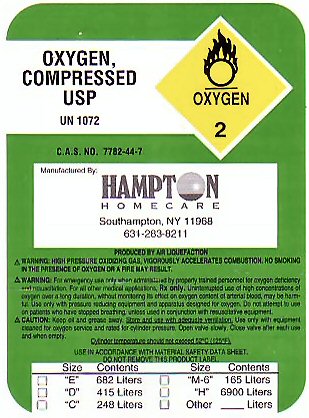 DRUG LABEL: OXYGEN
NDC: 65067-321 | Form: GAS
Manufacturer: Hampton Homecare
Category: prescription | Type: HUMAN PRESCRIPTION DRUG LABEL
Date: 20100101

ACTIVE INGREDIENTS: OXYGEN 99 L/100 L

OXYGEN COMPRESSED LABEL

OXYGEN COMPRESSED USP OXYGEN-2 UN 1072 C.A.S. NO. 7782-44-7

PRODUCED BY AIR LIQUEFACTION

WARNING: FOR EMERGENCY USE ONLY WHEN ADMINISTERED BY PROPERLY TRAINED PERSONNEL FOR OXYGEN DEFICIENCY AND RESUSCITATION. FOR ALL OTHER MEDICAL APPLICATIONS Rx ONLY. UNINTERRUPTED USE OF HIGH CONCENTRATIONS OF OXYGEN OVER A LONG DURATION WITHOUT MONITORING ITS EFFECT ON OXYGEN CONTENT OF ARTERIAL BLOOD MAY BE HARMFUL. USE ONLY WITH PRESSURE REDUCING EQUIPMENT AND APPARATUS DESIGNED FOR OXYGEN. DO NOT ATTEMPT TO USE ON PATIENTS WHO HAVE STOPPED BREATHING UNLESS USED IN CONJUNCTION WITH RESUSCITATIVE EQUIPMENT.

SIZE CONTENTS

E 682 LITERS

D 415 LITERS

C 248 LITERS

M-6 165 LITERS

H 6900 LITERS

OTHER ___________ LITERS

PRODUCT WARNINGS AND PRECAUTIONS

WARNING: HIGH PRESSURE OXIDIZING GAS, VIGOROUSLY ACCELERATES COMBUSTION. NO SMOKING IN THE PRESENCE OF OXYGEN OR A FIRE MAY RESULT. CAUTION: KEEP OIL AND GREASE AWAY. STORE AND USE WITH ADEQUATE VENTILATION. USE ONLY WITH EQUIPMENT CLEANED FOR OXYGEN SERVICE AND RATED FOR CYLINDER PRESSURE. OPEN VALVE SLOWLY. CLOSE VALVE AFTER EACH USE AND WHEN EMPTY. CYLINDER TEMPERATURE SHOULD NOT EXCEED 52 C (125 F) USE IN ACCORDANCE WITH MATERIAL SAFETY DATA SHEET. DO NOT REMOVE THIS PRODUCT LABEL.